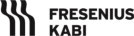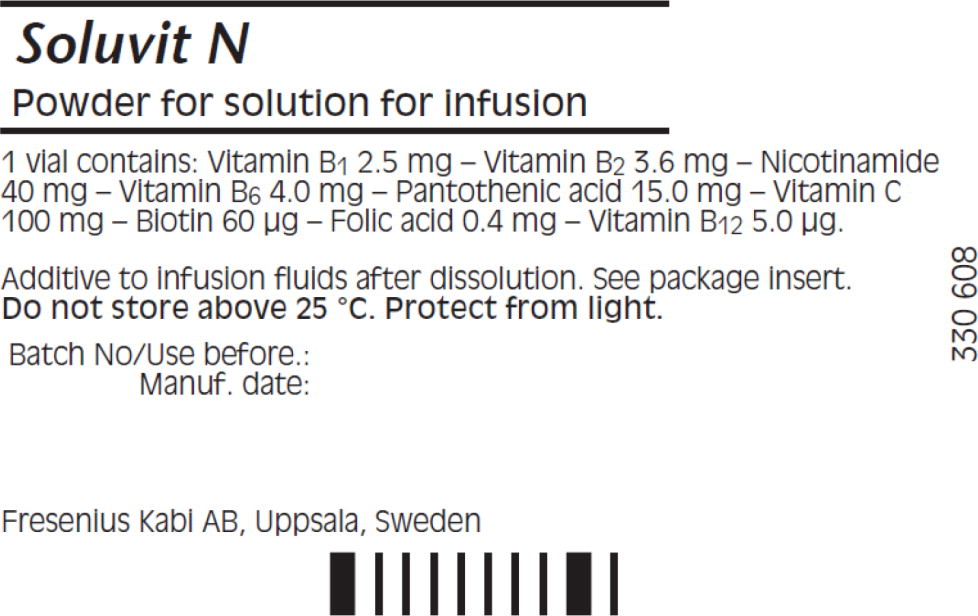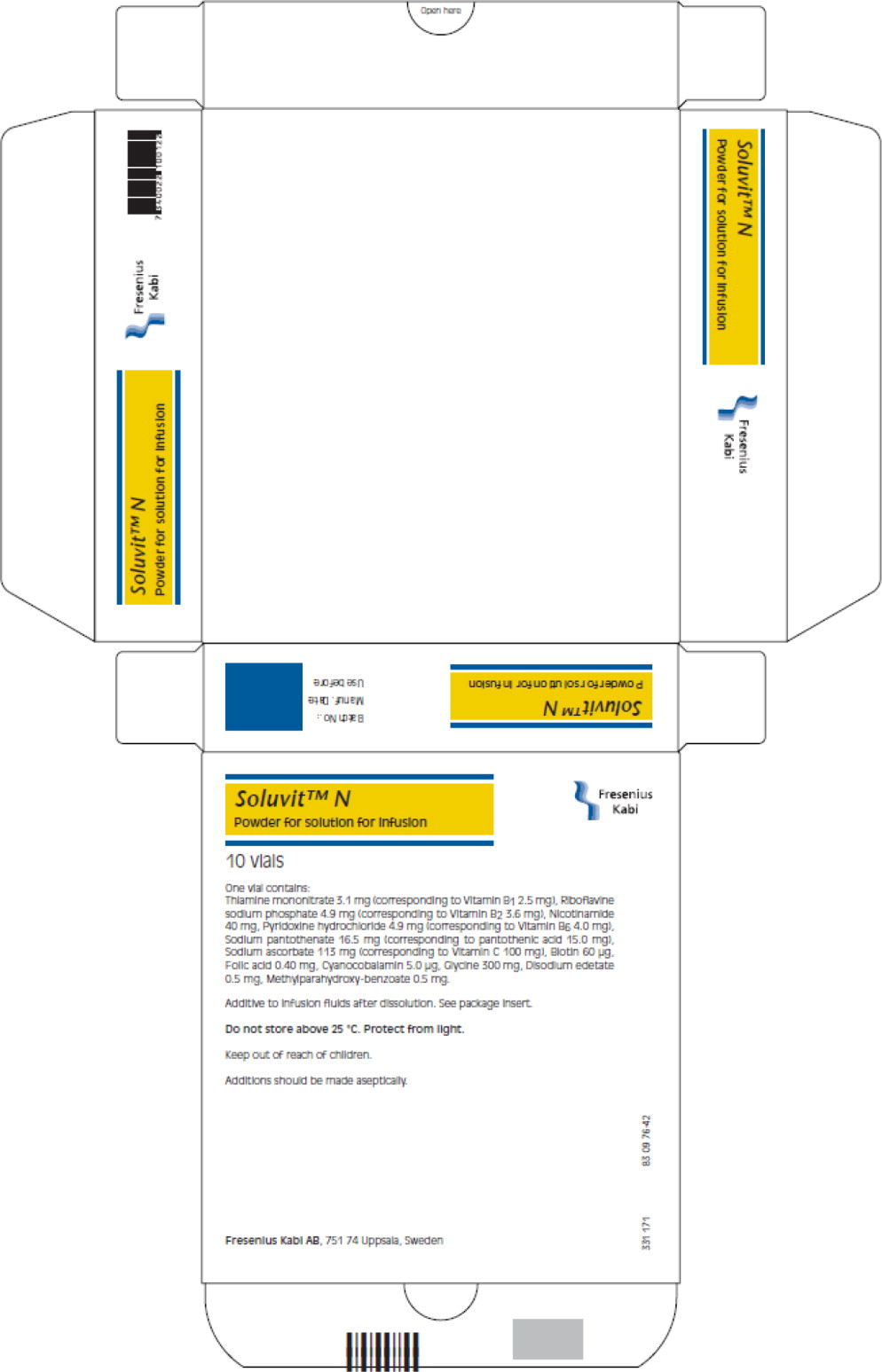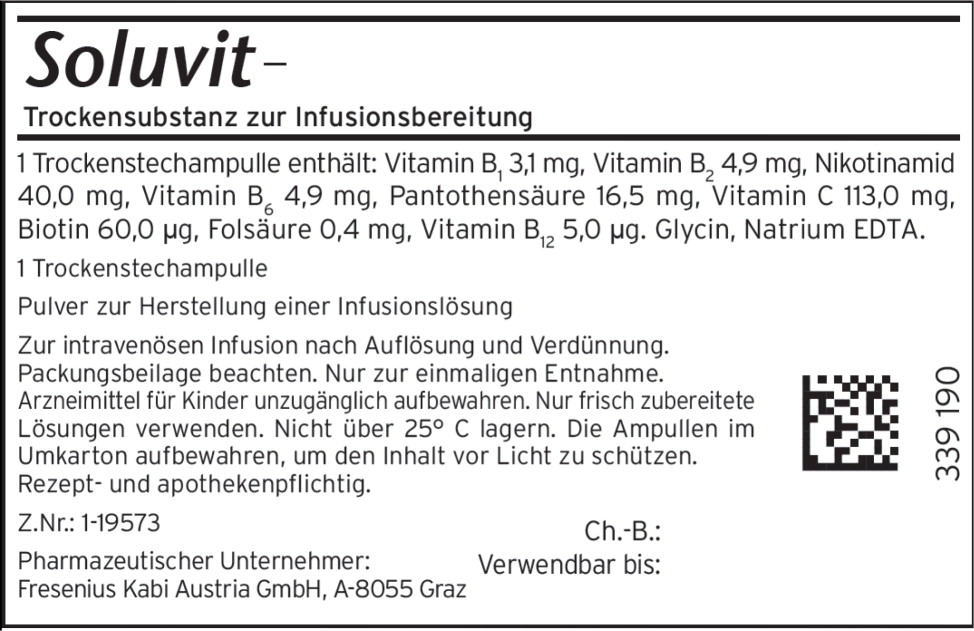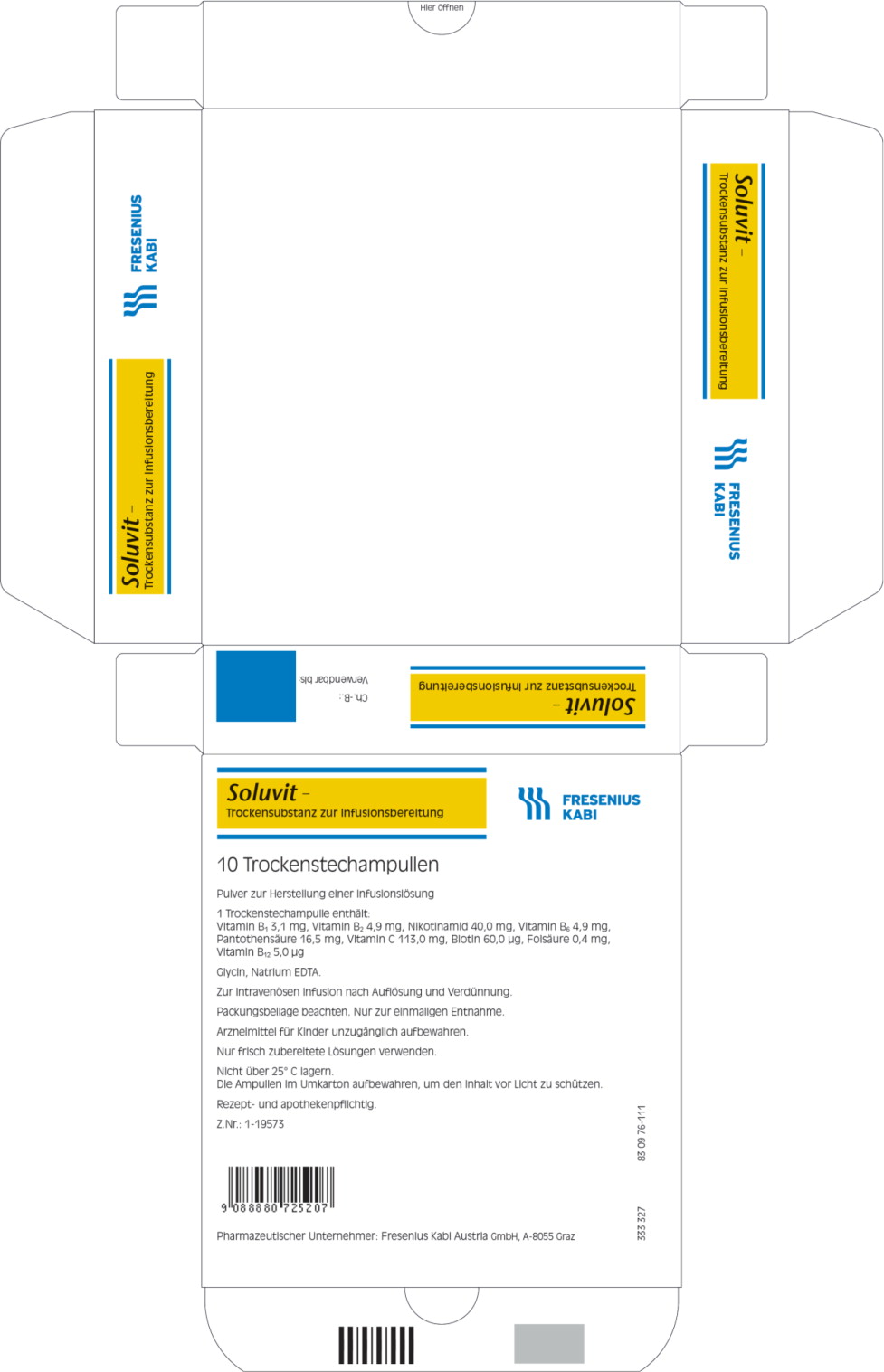 DRUG LABEL: SOLUVIT N
NDC: 65219-077 | Form: POWDER, FOR SOLUTION
Manufacturer: Fresenius Kabi USA, LLC
Category: prescription | Type: HUMAN PRESCRIPTION DRUG LABEL
Date: 20240606

ACTIVE INGREDIENTS: thiamine mononitrate 1.581 mg/1 mL; riboflavin 5'-phosphate sodium anhydrous 2.45 mg/1 mL; niacinamide 20.0 mg/1 mL; pyridoxine hydrochloride 2.45 mg/1 mL; folic acid 0.216 mg/1 mL; cyanocobalamin 2.775 ug/1 mL; sodium pantothenate 8.25 mg/1 mL; biotin 30.0 ug/1 mL; sodium ascorbate 56.5 mg/1 mL
INACTIVE INGREDIENTS: edetate disodium; glycine; water; methylparaben

Soluvit N
Powder for solution for infusion

Presentation

Soluvit N is a lyophilized, sterile, yellow mixture of water soluble vitamins for intravenous infusion. Qualitative and Quantitative Composition

ACTIVE INGREDIENT

One vial of Soluvit N contains:

Active ingredients | Quantity | 1 ml of reconstituted
Thiamine |  | Soluvit N contains:
mononitrate (Corresponding to Vitamin B1 2.5 mg) Riboflavine sodium | 3.1 mg | 0.31 mg
phosphate (Corresponding to Vitamin B2 3.6 mg) | 4.9 mg | 0.49 mg
Nicotinamide Pyridoxine | 40 mg | 4.0 mg
hydrochloride (corresponding to Vitamin B6 4.0 mg) Sodium | 4.9 mg | 0.49 mg
pantothenate (corresponding to pantothenic acid 15.0 mg) | 16.5 mg | 1.65 mg
Sodium ascorbate (corresponding to Vitamin C 100 mg) | 113 mg | 11.3 mg
Biotin | 60 μg | 6.0 μg
Folic acid | 0.40 mg | 40 μg
Cyanocobalamin | 5.0 μg | 0.5 μg

For the full list of excipients, see section list of excipients.

- Osmolality in 10 ml of water: approx. 490 mosm/kg water
- pH in 10 ml of water: 5.8

Therapeutic indications

Soluvit N is indicated in adult patients and children as a supplement in intravenous nutrition to meet the daily requirements of water soluble vitamins.

Posology and method of administration

Posology

Adults:

For adult patients and children weighing 10 kg or more, the recommended daily dosage is the content of one vial.

Infants:

Children weighing less than 10 kg should be given 1/10 of the content of one vial per kg body weight per day.

Contraindications

Known hypersensitivity to any of the components, e.g. thiamine or methyl parahydroxybenzoate.

Special warning and special precaution for use

Soluvit N must not be given undiluted.

When Soluvit N is diluted with water based solutions, the admixture should be protected from light. This is not necessary if Soluvit N is diluted with Intralipid because of the protective effect of the fat emulsion.

Interference with clinical laboratory tests

Biotin may interfere with laboratory tests that are based on a biotin/streptavidin interaction, leading to either falsely decreased or falsely increased test results, depending on the assay. The risk of interference is higher in children and patients with renal impairment and increases with higher doses. When interpreting results of laboratory tests, possible biotin interference has to be taken into consideration, especially if a lack of coherence with the clinical presentation is observed (e.g. thyroid test results mimicking Graves' disease in asymptomatic patients taking biotin or false negative troponin test results in patients with myocardial infarction taking biotin). Alternative tests not susceptible to biotin interference should be used, if available, in cases where interference is suspected. The laboratory personnel should be consulted when ordering laboratory tests in patients taking biotin.

Interaction with other medicinal products and other forms of interaction

Folic acid may lower the serum concentration of phenytoin and obscure pernicious anaemia.

Vitamin B6 can reduce the effect of levodopa.

Fertility, pregnancy and lactation

Animal reproduction studies or clinical investigations during pregnancy have not been carried out with Soluvit N. There are, however, published reports on safe administration of water soluble vitamins in this patient group.

Effects on ability to drive and use machines

Not relevant.

Undesirable effects

Allergic reactions including severe (anaphylactic) reactions may occur in patients hypersensitive to any component of the preparation, e.g. folic acid, thiamine or methyl parahydroxybensoate (frequency not known).

Reporting of suspected adverse reactions

Reporting suspected adverse reactions after authorisation of the medicinal product is important. It allows continued monitoring of the benefit/risk balance of the medicinal product. Healthcare professionals are asked to report any suspected adverse reactions via the national reporting system.

Overdose

No adverse effects of an overdose of water soluble vitamins have been reported, with exception of cases of extremly high parenteral doses. Overdoses caused by parenteral preparations for nutritional supplement of water soluble vitamins have not been reported.

No specific treatment is needed. See also section Contraindications.

List of excipients

Glycine (Aminoacetic acid)

Disodium edetate.

Methyl parahydroxybenzoate

Incompatibilities

Soluvit N may only be added to or mixed with other medicinal products for which compatibility has been documented.

Shelf-life of the medicinal product as packed for sale

18 months

Shelf-life after mixing

Chemical and physical in-use stability after dilution has been demonstrated for 24 hours at 25°C. From a microbiological point of view, the product should be used immediately. If not used immediately, in-use storage times and conditions prior to use are the responsibility of the user and would normally not be longer than 24 hours at 2-8°C, unless mixing has taken place in controlled and validated aseptic conditions.

Special precautions for storage

Do not store above 25°C. Protect from light.

Instructions for use/handling, and disposal

Adults and children age 11 years and above:

The contents of one vial of Soluvit N are dissolved by adding 10 ml of:

1. Vitalipid N Adult

or 2. Intralipid 10%, Intralipid 20%, Intralipid 30%, Structolipid

or 3. Water for Injections

or 4. Glucose solution for infusion (5%-50%)

Soluvit N may be added to parenteral nutrition admixtures containing carbohydrates, lipids, amino acids, electrolytes and trace elements provided that compatibility and stability have been confirmed.

Children below 11 years of age:

The contents of one vial are dissolved by adding 10 ml of:

1. Vitalipid N Infant (for children above 10 kg/bw)

or 2. Intralipid 10%, Intralipid 20%

or 3. Water for Injections

or 4. Glucose solution for infusion (5%-50%)

Children weighing less than 10 kg should be given 1 ml of the dissolved mixture per kg body weight per day. Children weighing 10 kg or more should be given 10 ml (one vial) per day.

Due to differences in the dosage regimes for Soluvit N and Vitalipid N Infant, the mixture 1 is not recommended for children weighing less than 10 kg.

Soluvit N may be added to parenteral nutrition admixtures containing carbohydrates, lipids, amino acids, electrolytes and trace elements provided that compatibility and stability have been confirmed.

Disposal

Any unused medicinal product or waste material should be disposed of in accordance with local requirements.

Manufacturer:

Fresenius Kabi AB, Uppsala, Sweden

March 2019

PACKAGE LABEL – PRINCIPAL DISPLAY – Soluvit N Vial Label

Soluvit N

Powder for solution for infusion

PACKAGE LABEL – PRINCIPAL DISPLAY – Soluvit N Carton

Soluvit™ N

Powder for solution for infusion

10 Vials

PACKAGE LABEL – PRINCIPAL DISPLAY – Soluvit N Vial Label

Soluvit -
Trockensubstanz zur Infusionsbereitung

PACKAGE LABEL – PRINCIPAL DISPLAY – Soluvit N Carton

Soluvit -
Trockensubstanz zur Infusionsbereitung
10 Trockenstechampullen